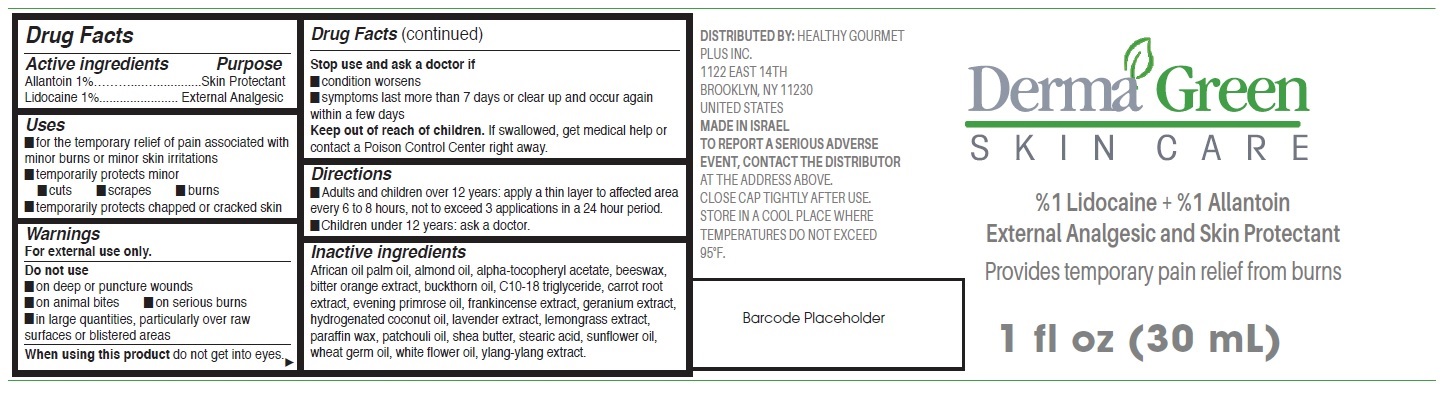 DRUG LABEL: DermaGreen Skin Care
NDC: 83363-003 | Form: CREAM
Manufacturer: Healthy Gourmet Plus, Inc
Category: otc | Type: HUMAN OTC DRUG LABEL
Date: 20231215

ACTIVE INGREDIENTS: ALLANTOIN 10 mg/1 mL; LIDOCAINE 10 mg/1 mL
INACTIVE INGREDIENTS: ALMOND OIL; YELLOW WAX; CITRUS AURANTIUM FRUIT RIND; C10-18 TRIGLYCERIDES; CARROT; EVENING PRIMROSE OIL; FRANKINCENSE; GERANIUM ROBERTIANUM LEAF; HYDROGENATED COCONUT OIL; LAVANDULA ANGUSTIFOLIA SUBSP. ANGUSTIFOLIA FLOWER; PARAFFIN; POGOSTEMON CABLIN LEAF OIL; SHEA BUTTER; STEARIC ACID; SUNFLOWER OIL; WHEAT GERM OIL

DermaGreen Skin Care

Active ingredients

Allantoin 1%

Lidocaine 1%

Purpose

Skin Protectant

External Analgesic

Uses

- for the temporary relief of pain associated with minor burns or minor skin irritations
- temporarily protects minor
- cuts
- scrapes
- burns
- temporarily protects chapped or cracked skin

Warnings

For external use only.

Do not use

- on deep or puncture wounds
- on animal bites
- on serious burns
- in large quantities, particularly over raw surfaces or blistered areas

When using this product

do not get into eyes.

Stop use and ask a doctor if

- condition worsens
- symptoms last more than 7 days or clear up and occur again within a few days

Keep out of reach of children.

If swallowed, get medical help or contact a Poison Control Center right away.

Directions

- Adults and children over 12 years: apply a thin layer to affected area every 6 to 8 hours, not to exceed 3 applications in a 24 hour period.
- Children under 12 years: ask a doctor.

Inactive ingredients

African oil palm oil, almond oil, alpha-tocopheryl acetate, beeswax, bitter orange extract, buckthorn oil, C10-18 triglyceride, carrot root extract, evening primrose oil, frankincense extract, geranium extract, hydrogenated coconut oil, lavender extract, lemongrass extract, paraffin wax, patchouli oil, shea butter, stearic acid, sunflower oil, wheat germ oil, white flower oil, ylang-ylang extract.